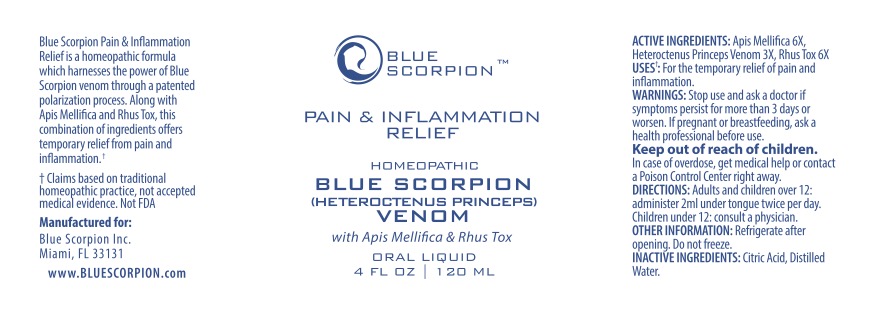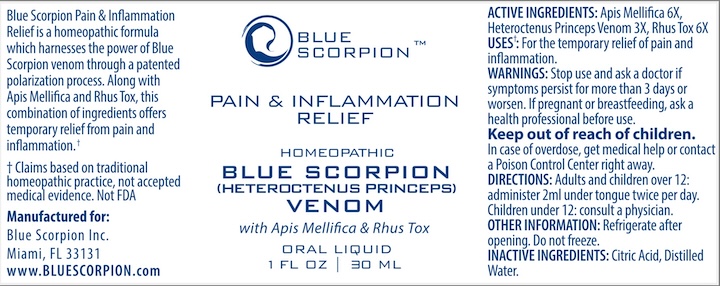 DRUG LABEL: Blue Scorpion Pain and Inflammation Relief
NDC: 83627-901 | Form: LIQUID
Manufacturer: Blue Scorpion Inc.
Category: homeopathic | Type: HUMAN OTC DRUG LABEL
Date: 20240116

ACTIVE INGREDIENTS: APIS MELLIFERA 6 [hp_X]/1 mL; TOXICODENDRON PUBESCENS LEAF 6 [hp_X]/1 mL; RHOPALURUS PRINCEPS VENOM 3 [hp_X]/1 mL
INACTIVE INGREDIENTS: CITRIC ACID MONOHYDRATE; WATER

Blue Scorpion Pain and Inflammation Relief

ACTIVE INGREDIENTS:

Apis Mellifica 6X

Heteroctenus Princeps Venom 3X

Rhus Tox 6X

DIRECTIONS:

Adults and children 12 years and over: | Administer 2 ml under tongue twice per day.
Children under 12: | Consult a physician.

INACTIVE INGREDIENTS:

Citric Acid, Distilled water

KEEP OUT OF REACH OF CHILDREN: In case of overdose, get medical help or call a Poison Control Center right away.

INDICATIONS:

Uses

- For the temporary relief of pain and inflammation

PURPOSE:

Hereroctenus princeps venom 3x.....Pain, inflammation
Apis Mellifica 6X ..............................Pain, inflammation
Rhus Tox 6X.....................................Pain, inflammation

If pregnant or breast feeding, ask a health professional before use.

Stop use and ask a doctor if symptoms persist for more than 3 days or worsen.

OTHER INFORMATION:

- Refrigerate after opening
- Do not freeze

Warning

Stop use and ask doctor if symptoms persist for more than 3 days or worsen.

PACKAGE LABEL DISPLAY:

Principal display panel